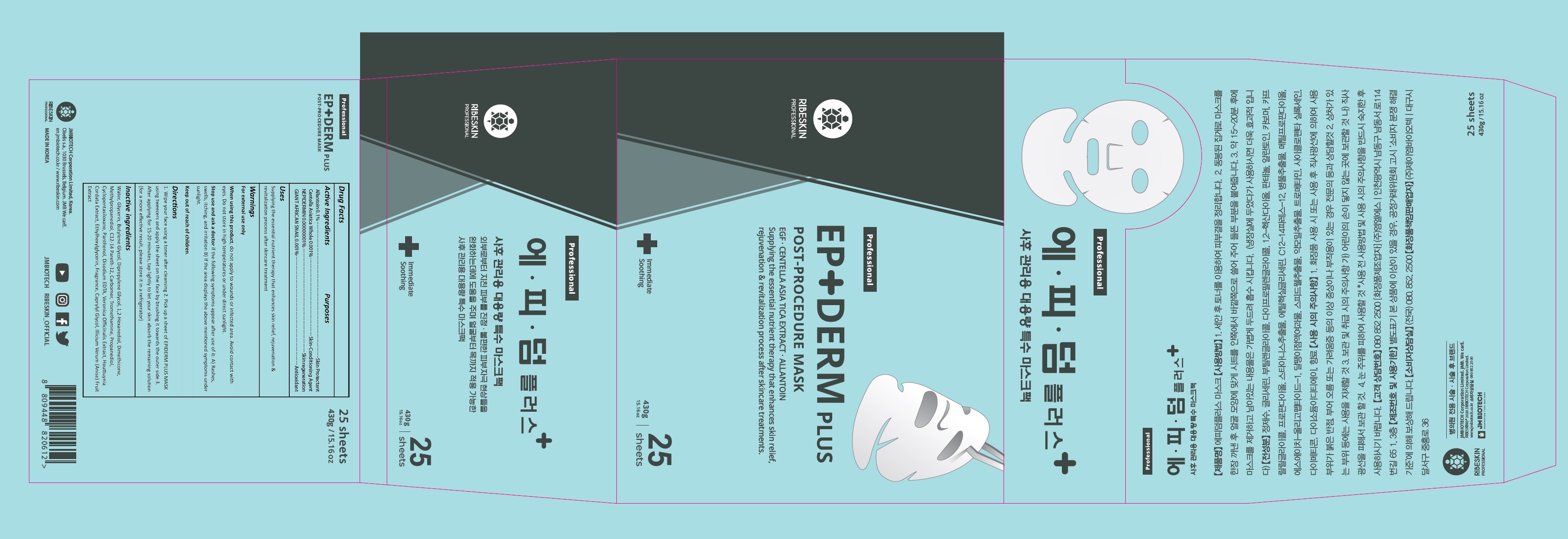 DRUG LABEL: RIBESKIN EPIDERM PLUS MASK
NDC: 82224-001 | Form: CREAM
Manufacturer: JM Bio-Tech Co., Ltd.
Category: otc | Type: HUMAN OTC DRUG LABEL
Date: 20211027

ACTIVE INGREDIENTS: ALLANTOIN 0.1 g/100 g; CENTELLA ASIATICA WHOLE 0.001 g/100 g; NEPIDERMIN 0.00000001 g/100 g; GIANT AFRICAN SNAIL 0.001 g/100 g
INACTIVE INGREDIENTS: WATER; GLYCERIN; BUTYLENE GLYCOL; 1,2-HEXANEDIOL; DIMETHICONE; METHYLPROPANEDIOL; C12-14 PARETH-12; CARBOMER HOMOPOLYMER, UNSPECIFIED TYPE; TROMETHAMINE; PROPANEDIOL; CYCLOMETHICONE 5; PANTHENOL; EDETATE DISODIUM ANHYDROUS; HOUTTUYNIA CORDATA FLOWERING TOP; ETHYLHEXYLGLYCERIN; CAPRYLYL GLYCOL; STAR ANISE FRUIT

82224-001

ACTIVE INGREDIENT

Allantoin 0.1%

Centella Asiatica Whole 0.001%

Nepidermin 0.00000001%

Giant African Snail 0.001%

PURPOSE

Skin Protectant, Skin-conditioning agent, skin regeneration, antioxidant

INDICATIONS AND USAGE

Supplying the essential nutrient therapy that enhances skin relief, rejuvenation & revitalization process after skincare treatment.

DOSAGE AND ADMINISTRATION

1. Wipe your face using a toner after cleansing 2. Pick up a sheet of EPIDERM PLUS MASK using tweezers and apply the sheet on the face by brushing it towards the outer side 3. After applying for 15-20 minutes, tap lightly to let your skin absorb the remaining solution (for a more effective result, please store it in a refrigerator)

WARNINGS

For external use only
When using this product, do not apply to wounds or infected area. Avoid contact with eyes. Do not store in high temperatures or under direct sunlight.
Stop use and ask a doctor if the following symptoms appear after use of it: A) Rashes, swells, itching, and irritation B) If the area displays the above mentioned symptoms under sunlight.
Keep out of reach of children.

Keep out of reach of the children.

INACTIVE INGREDIENT

Water, Glycerin, Butylene Glycol, Dipropylene Glycol, 1,2-Hexanediol, Dimethicone, Methylpropanediol, C12-14 Pareth-12, Carbomer, Tromethamine, Propanediol, Cyclopentasiloxane, Panthenol, Disodium EDTA, Snail Secretion Filtrate, Veronica Officinalis Extract, Houttuynia Cordata Extract, Ethylhexylglycerin, Fragrance, Caprylyl Glycol, Illicium Verum (Anise) Fruit Extract, sh-Oligopeptide-1